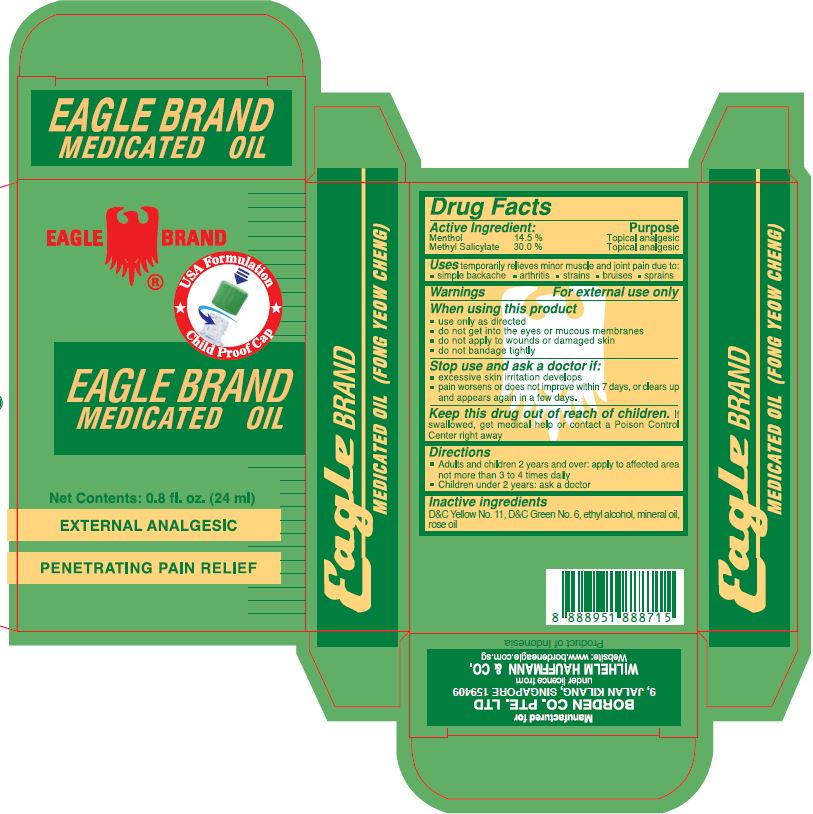 DRUG LABEL: Eagle
NDC: 60954-002 | Form: OIL
Manufacturer: Eagle Indo Pharma, PT
Category: otc | Type: HUMAN OTC DRUG LABEL
Date: 20241007

ACTIVE INGREDIENTS: MENTHOL 14.5 g/100 mL; METHYL SALICYLATE 30 g/100 mL
INACTIVE INGREDIENTS: D&C YELLOW NO. 11; ALCOHOL; MINERAL OIL; ROSE OIL; D&C GREEN NO. 6

Eagle Brand Medicated Oil

Active Ingredient

Menthol 14.5%
Methyl Salicylate 30.0%

Purpose

Topical Analgesic

Topical Analgesic

Uses

temporarily relieves minor muscle and joint pain due to : ■simple backache ■ arthritis ■ strains ■ bruises

■ sprains

Warnings

For external use only

When using this product

■ use only as directed

■ do not get into eyes or mucous membranes

■ do not apply to wound or damaged skin.

■ do not bandage tightly

Stop use and ask a doctor if

■ excessive skin irritation develops

■ pain worsens or does not improve within 7 days, or clears up and appears again in a few days

Keep this drug out of reach of children

If swallowed, get medical help or contact a Poison Control Center right away.

Directions

■ Adults and children 2 years and over: apply to affected area not more than 3 to 4 time daily.

■ Children under 2 years of age: ask a doctor

Inactive ingredients

D&C Yellow No. 11, D&C Green No. 6, ethyl alcohol, mineral oil, rose oil